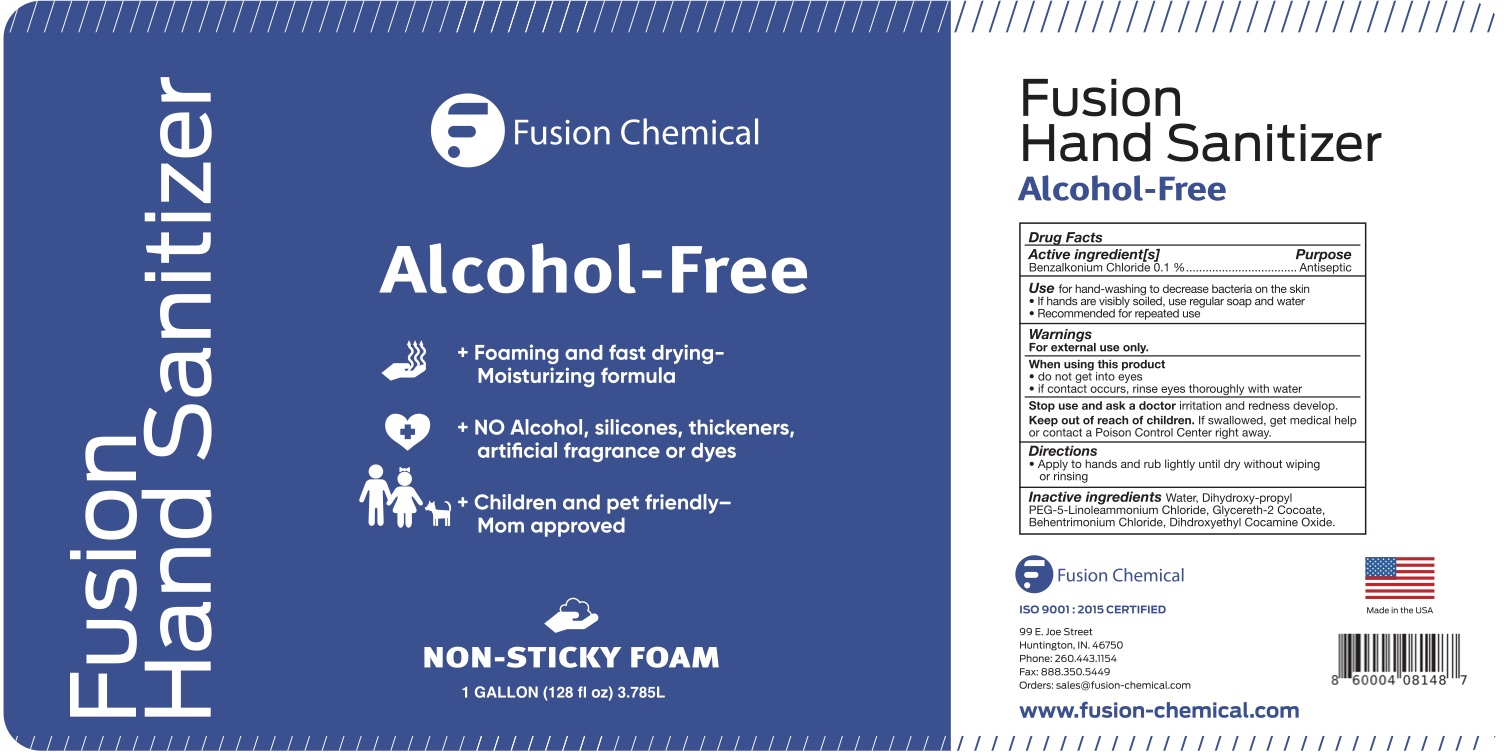 DRUG LABEL: Servo Stat BAC
NDC: 78041-0023 | Form: LIQUID
Manufacturer: Fusion Chemcial
Category: otc | Type: HUMAN OTC DRUG LABEL
Date: 20241126

ACTIVE INGREDIENTS: BENZALKONIUM CHLORIDE 1 mg/1 mL
INACTIVE INGREDIENTS: BEHENTRIMONIUM CHLORIDE; DIHYDROXYETHYL COCAMINE OXIDE; GLYCERETH-2 COCOATE; WATER; DIHYDROXYPROPYL PEG-5 LINOLEAMMONIUM CHLORIDE

78041-0023

ACTIVE INGREDIENT

Benzalkonium Chloride 0.1%

INACTIVE INGREDIENT

Water, Dihydroxy-propyl PEG-5-Linoleammonium Chloride, Glycereth-2 Cocoate, Behentrimonium Chloride, Dihdroxyethyl Cocamine Oxide.

WARNINGS

For external use only - When using this product - do not get into eyes - if contact occurs, rinse eyes thoroughly with water - Stop use and ask a doctor if - irritation and redness ...

DOSAGE AND ADMINISTRATION

Apply to hands and rub lightly until dry without wiping or rinsing

INDICATIONS AND USAGE

USE FOR HAND-WASHING TO DECREASE BACTERIA ON THE SKIN

If hands are visibly soiled, use regular soap and water
Recommended for repeated use

Keep out of reach of children. If swallowed, get medical help or contact a Poison Control Center right away

PURPOSE

Antiseptic